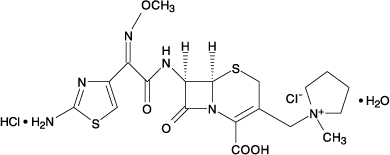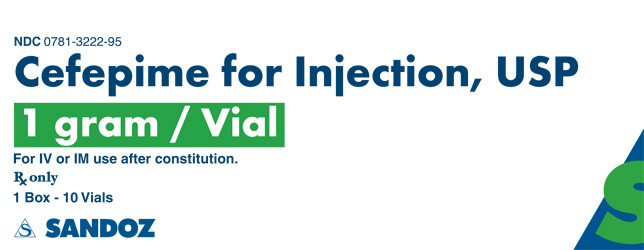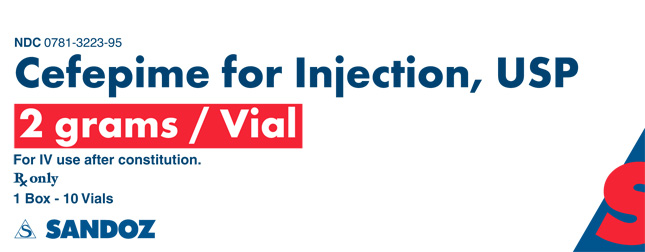 DRUG LABEL: Cefepime Hydrochloride
NDC: 0781-3222 | Form: INJECTION, POWDER, FOR SOLUTION
Manufacturer: Sandoz Inc
Category: prescription | Type: HUMAN PRESCRIPTION DRUG LABEL
Date: 20150416

ACTIVE INGREDIENTS: CEFEPIME HYDROCHLORIDE 1 g/1 1
INACTIVE INGREDIENTS: ARGININE

Cefepime for Injection, USP

For Intravenous or Intramuscular Use

To reduce the development of drug-resistant bacteria and maintain the effectiveness of cefepime for injection and other antibacterial drugs, cefepime for injection should be used only to treat or prevent infections that are proven or strongly suspected to be caused by bacteria.

DESCRIPTION

Cefepime for injection, USP is a semi-synthetic, broad spectrum, cephalosporin antibiotic for parenteral administration. The chemical name is 1-[[(6R,7R)-7-[2-(2-amino-4-thiazolyl)-glyoxylamido]-2-carboxy-8-oxo-5-thia-1-azabicyclo [4.2.0]oct-2-en-3-yl]methyl]-1-methylpyrrolidinium chloride, 7^2-(Z)-(O-methyloxime), monohydrochloride, monohydrate, which corresponds to the following structural formula:

Cefepime hydrochloride is a white to pale yellow powder. Cefepime hydrochloride contains the equivalent of not less than 825 mcg and not more than 911 mcg of cefepime (C19H24N6O5S2) per mg, calculated on an anhydrous basis. It is highly soluble in water.

Cefepime for injection, USP is supplied for intramuscular or intravenous administration in strengths equivalent to 1 g, and 2 g of cefepime. (See DOSAGE AND ADMINISTRATION.) Cefepime for injection, USP is a sterile, dry mixture of cefepime hydrochloride and L-arginine. It contains the equivalent of not less than 90 percent and not more than 115 percent of the labeled amount of cefepime (C19H24N6O5S2).

The L-arginine, at an approximate concentration of 707 mg/g of cefepime, is added to control the pH of the constituted solution at 4 to 6. Freshly constituted solutions of cefepime for injection, USP will range in color from pale yellow to amber.

CLINICAL PHARMACOLOGY

Cefepime is an antibacterial agent belonging to the cephalosporin class of antibacterials with in vitro antibacterial activity against facultative Gram-positive and Gram-negative bacteria.

Pharmacokinetics

The average plasma concentrations of cefepime observed in healthy adult male volunteers (n=9) at various times following single 30-minute infusions (IV) of cefepime 500 mg, 1 g, and 2 g are summarized in Table 1. Elimination of cefepime is principally via renal excretion with an average (±SD) half-life of 2 (±0.3) hours and total body clearance of 120 (±8) mL/min in healthy volunteers. Cefepime pharmacokinetics are linear over the range 250 mg to 2 g. There is no evidence of accumulation in healthy adult male volunteers (n=7) receiving clinically relevant doses for a period of 9 days.

Absorption

The average plasma concentrations of cefepime and its derived pharmacokinetic parameters after intravenous (IV) administration are portrayed in Table 1.

Table 1: Average Plasma Concentrations in mcg/mL of Cefepime and Derived Pharmacokinetic Parameters (±SD), Intravenous Administration
 | Cefepime for injection
Parameter | 500 mg IV | 1 g IV | 2 g IV
0.5 h | 38.2 | 78.7 | 163.1
1 h | 21.6 | 44.5 | 85.8
2 h | 11.6 | 24.3 | 44.8
4 h | 5 | 10.5 | 19.2
8 h | 1.4 | 2.4 | 3.9
12 h | 0.2 | 0.6 | 1.1
Cmax, mcg/mL | 39.1 (3.5) | 81.7 (5.1) | 163.9 (25.3)
AUC, h•mcg/mL | 70.8 (6.7) | 148.5 (15.1) | 284.8 (30.6)
Number of subjects (male) | 9 | 9 | 9

Following intramuscular (IM) administration, cefepime is completely absorbed. The average plasma concentrations of cefepime at various times following a single intramuscular injection are summarized in Table 2. The pharmacokinetics of cefepime are linear over the range of 500 mg to 2 g intramuscularly and do not vary with respect to treatment duration.

Table 2: Average Plasma Concentrations in mcg/mL of Cefepime and Derived Pharmacokinetic Parameters (±SD), Intramuscular Administration
 | Cefepime for injection
Parameter | 500 mg IM | 1 g IM | 2 g IM
0.5 h | 8.2 | 14.8 | 36.1
1 h | 12.5 | 25.9 | 49.9
2 h | 12 | 26.3 | 51.3
4 h | 6.9 | 16 | 31.5
8 h | 1.9 | 4.5 | 8.7
12 h | 0.7 | 1.4 | 2.3
Cmax, mcg/mL | 13.9 (3.4) | 29.6 (4.4) | 57.5 (9.5)
Tmax, h | 1.4 (0.9) | 1.6 (0.4) | 1.5 (0.4)
AUC, h•mcg/mL | 60 (8) | 137 (11) | 262 (23)
Number of subjects (male) | 6 | 6 | 12

Distribution

The average steady-state volume of distribution of cefepime is 18 (±2) L. The serum protein binding of cefepime is approximately 20% and is independent of its concentration in serum.

Cefepime is excreted in human milk. A nursing infant consuming approximately 1000 mL of human milk per day would receive approximately 0.5 mg of cefepime per day. (See PRECAUTIONS: Nursing Mothers.)

Concentrations of cefepime achieved in specific tissues and body fluids are listed in Table 3.

Table 3: Average Concentrations of Cefepime in Specific Body Fluids (mcg/mL) or Tissues (mcg/g)
Tissue or Fluid | Dose/ Route | # of Patients | Average Time of Sample Post-Dose (h) | Average Concentration
Blister Fluid | 2 g IV | 6 | 1.5 | 81.4 mcg/mL
Bronchial Mucosa | 2 g IV | 20 | 4.8 | 24.1 mcg/g
Sputum | 2 g IV | 5 | 4 | 7.4 mcg/mL
Urine | 500 mg IV | 8 | 0 to 4 | 292 mcg/mL
 | 1 g IV | 12 | 0 to 4 | 926 mcg/mL
 | 2 g IV | 12 | 0 to 4 | 3120 mcg/mL
Bile | 2 g IV | 26 | 9.4 | 17.8 mcg/mL
Peritoneal Fluid | 2 g IV | 19 | 4.4 | 18.3 mcg/mL
Appendix | 2 g IV | 31 | 5.7 | 5.2 mcg/g
Gallbladder | 2 g IV | 38 | 8.9 | 11.9 mcg/g
Prostate | 2 g IV | 5 | 1 | 31.5 mcg/g

Data suggest that cefepime does cross the inflamed blood-brain barrier. The clinical relevance of these data is uncertain at this time.

Metabolism and Excretion

Cefepime is metabolized to N-methylpyrrolidine (NMP) which is rapidly converted to the N-oxide (NMP-N-oxide). Urinary recovery of unchanged cefepime accounts for approximately 85% of the administered dose. Less than 1% of the administered dose is recovered from urine as NMP, 6.8% as NMP-N-oxide, and 2.5% as an epimer of cefepime. Because renal excretion is a significant pathway of elimination, patients with renal dysfunction and patients undergoing hemodialysis require dosage adjustment. (See DOSAGE AND ADMINISTRATION.)

Specific Populations

Renal impairment

Cefepime pharmacokinetics have been investigated in patients with various degrees of renal impairment (n=30). The average half-life in patients requiring hemodialysis was 13.5 (±2.7) hours and in patients requiring continuous peritoneal dialysis was 19 (±2) hours. Cefepime total body clearance decreased proportionally with creatinine clearance in patients with abnormal renal function, which serves as the basis for dosage adjustment recommendations in this group of patients. (See DOSAGE AND ADMINISTRATION.)

Hepatic impairment

The pharmacokinetics of cefepime were unaltered in patients with hepatic impairment who received a single 1 g dose (n=11).

Geriatric patients

Cefepime pharmacokinetics have been investigated in elderly (65 years of age and older) men (n=12) and women (n=12) whose mean (SD) creatinine clearance was 74 (±15) mL/min. There appeared to be a decrease in cefepime total body clearance as a function of creatinine clearance. Therefore, dosage administration of cefepime in the elderly should be adjusted as appropriate if the patient’s creatinine clearance is 60 mL/min or less. (See DOSAGE AND ADMINISTRATION.)

Pediatric patients

Cefepime pharmacokinetics have been evaluated in pediatric patients from 2 months to 11 years of age following single and multiple doses on every 8 hours (n=29) and every 12 hours (n=13) schedules. Following a single intravenous dose, total body clearance and the steady-state volume of distribution averaged 3.3 (±1) mL/min/kg and 0.3 (±0.1) L/kg, respectively. The urinary recovery of unchanged cefepime was 60.4 (±30.4)% of the administered dose, and the average renal clearance was 2 (±1.1) mL/min/kg. There were no significant effects of age or gender (25 male vs 17 female) on total body clearance or volume of distribution, corrected for body weight. No accumulation was seen when cefepime was given at 50 mg per kg every 12 hours (n=13), while Cmax, AUC, and t1/2 were increased about 15% at steady state after 50 mg per kg every 8 hours. The exposure to cefepime following a 50 mg per kg intravenous dose in a pediatric patient is comparable to that in an adult treated with a 2 g intravenous dose. The absolute bioavailability of cefepime after an intramuscular dose of 50 mg per kg was 82.3 (±15)% in eight patients.

Microbiology

Mechanism of Action

Cefepime is a bactericidal agent that acts by inhibition of bacterial cell wall synthesis. Cefepime has a broad spectrum of in vitro activity that encompasses a wide range of Gram-positive and Gram-negative bacteria. Cefepime has a low affinity for chromosomally-encoded beta-lactamases. Cefepime is highly resistant to hydrolysis by most beta-lactamases and exhibits rapid penetration into Gram-negative bacterial cells. Within bacterial cells, the molecular targets of cefepime are the penicillin binding proteins (PBP).

Cefepime has been shown to be active against most isolates of the following microorganisms, both in vitro and in clinical infections as described in the INDICATIONS AND USAGE section.

Gram-negative bacteria

Enterobacter spp.

Escherichia coli

Klebsiella pneumoniae

Proteus mirabilis

Pseudomonas aeruginosa

Gram-positive bacteria

Staphylococcus aureus (methicillin-susceptible isolates only)

Streptococcus pneumoniae

Streptococcus pyogenes

Viridans group streptococci

The following in vitro data are available, but their clinical significance is unknown. At least 90 percent of the following bacteria exhibit an in vitro minimum inhibitory concentration (MIC) less than or equal to the susceptible breakpoint for cefepime. However, the efficacy of cefepime in treating clinical infections due to these bacteria has not been established in adequate and well-controlled clinical trials.

Gram-positive bacteria

Staphylococcus epidermidis (methicillin-susceptible isolates only)

Staphylococcus saprophyticus

Streptococcus agalactiae

NOTE: Most isolates of enterococci, e.g., Enterococcus faecalis, and methicillin-resistant staphylococci are resistant to cefepime.

Gram-negative bacteria

Acinetobactercalcoaceticus subsp. lwoffii

Citrobacterdiversus

Citrobacterfreundii

Enterobacteragglomerans

Haemophilusinfluenzae

Hafniaalvei

Klebsiellaoxytoca

Moraxella catarrhalis

Morganella morganii

Proteus vulgaris

Providencia rettgeri

Providencia stuartii

Serratia marcescens

NOTE: Cefepime is inactive against many isolates of Stenotrophomonasmaltophilia.

Susceptibility Tests Methods

When available, the clinical microbiology laboratory should provide the results of in vitro susceptibility test result for antimicrobial drug products used in resident hospitals to the physician as periodic reports that describe the susceptibility profile of nosocomial and community-acquired pathogens. These reports should aid the physician in selecting an antibacterial drug product for treatment.

Dilution Techniques

Quantitative methods are used to determine antimicrobial minimum inhibitory concentrations (MICs). These MICs provide estimates of the susceptibility of bacteria to antimicrobial compounds. The MICs should be determined using a standardized test method^(1, 2) (broth and/or agar). The MIC should be interpreted according to the criteria provided in Table 4.

Diffusion Techniques

Quantitative methods that require measurement of zone diameters can also provide reproducible estimates of the susceptibility of bacteria to antimicrobial compounds. The zone size provides an estimate of the susceptibility of bacteria to antimicrobial compounds. The zone size should be determined using a standardized test method.^2,3 This procedure uses paper discs impregnated with 30 mcg cefepime to test the susceptibility of microorganisms to cefepime. The disc diffusion interpretive criteria are provided in Table 4.

Table 4: Susceptibility Test Interpretive Criteria for Cefepime [For patients with renal impairment see Table 11 in Dosage and Administration]
Pathogen | Minimum Inhibitory Concentrations (mcg/mL) |  |  | Disk Diffusion Zone Diameters (mm)
Pathogen | (S) Susceptible | (I) Intermediate | (R) Resistant | (S) Susceptible | (I) Intermediate | (R) Resistant
Enterobacteriaceae | ≤2 | 4 to 8 [For isolates of Enterobacteriaceae with intermediate susceptibility, use a dose of 2 g every 8 hours in patients with normal renal function] | ≥16 | ≥25 | 19 to 24 | ≤18
Pseudomonas aeruginosa [For P. aeruginosa, use 2 g IV every 8 hours in patients with normal renal function] | ≤8 | - | ≥16 | ≥18 | - | ≤17
Streptococcus pneumoniae [For non-meningitis isolates, a penicillin MIC of ≤ 0.06 mcg/mL (or oxacillin zone ≥ 20 mm) can predict susceptibility to cefepime.] non-meningitis isolates | ≤1 | 2 | ≥4 | - | - | -
Streptococcus pyogenes | ≤0.5 | - | - | ≥24 | - | -
Viridans group streptococci | ≤1 | 2 | ≥4 | ≥24 | 22 to 23 | ≤21

Susceptibility of staphylococci to cefepime may be deduced from testing only penicillin and either cefoxitin or oxacillin.

A report of “Susceptible” indicates that the antimicrobial is likely to inhibit growth of the pathogen if the antimicrobial compound reaches the concentrations at the infection site necessary to inhibit growth of the pathogen. A report of “Intermediate” indicates that the results should be considered equivocal, and, if the microorganism is not fully susceptible to alternative, clinically feasible drugs, the test should be repeated. This category implies possible clinical applicability in body sites where the drug product is physiologically concentrated or in situations where a high dosage of the drug can be used. This category also provides a buffer zone that prevents small uncontrolled technical factors from causing major discrepancies in interpretation. A report of “Resistant” indicates that the antimicrobial is not likely to inhibit growth of the pathogen if the antimicrobial compound reaches the concentrations usually achievable at the infection site; other therapy should be selected.

Quality Control

Standardized susceptibility test procedures require the use of laboratory controls to monitor and ensure the accuracy and precision of supplies and reagents used in the assay, and the techniques of the individual performing the test.^1,2,3 Standard cefepime powder should provide the following range of MIC values noted in Table 5. For the diffusion technique using the 30 mcg disc, the criteria in Table 5 should be achieved.

Table 5: Acceptable Quality Control Ranges for Cefepime
QC Strain | Minimum Inhibitory Concentrations (mcg/mL) | Disk Diffusion (zone diameters in mm)
Escherichia coli ATCC 25922 | 0.015 to 0.12 | 31 to 37
Staphylococcus aureus ATCC 29213 | 1 to 4 | -
Staphylococcus aureus ATCC 25923 | - | 23 to 29
Pseudomonas aeruginosa ATCC 27853 | 0.5 to 4 | 24 to 30
Streptococcus pneumoniae ATCC 49619 | 0.03 to 0.25 | 28 to 35
Haemophilusinfluenzae ATCC 49247 | 0.5 to 2 | 25 to 31
Neisseria gonorrhoeae ATCC 49226 | 0.015 to 0.06 | 37 to 46

INDICATIONS AND USAGE

Cefepime for injection, USP is indicated in the treatment of the following infections caused by susceptible strains of the designated microorganisms (see also PRECAUTIONS: Pediatric Use and DOSAGE AND ADMINISTRATION):

Pneumonia (moderate to severe) caused by Streptococcus pneumoniae, including cases associated with concurrent bacteremia, Pseudomonas aeruginosa, Klebsiellapneumoniae, or Enterobacter species.

Empiric Therapy for Febrile Neutropenic Patients. Cefepime as monotherapy is indicated for empiric treatment of febrile neutropenic patients. In patients at high risk for severe infection (including patients with a history of recent bone marrow transplantation, with hypotension at presentation, with an underlying hematologic malignancy, or with severe or prolonged neutropenia), antimicrobial monotherapy may not be appropriate. Insufficient data exist to support the efficacy of cefepime monotherapy in such patients. (See CLINICAL STUDIES.)

Uncomplicated and Complicated Urinary Tract Infections (including pyelonephritis) caused by Escherichia coli or Klebsiellapneumoniae, when the infection is severe, or caused by Escherichia coli, Klebsiellapneumoniae, or Proteus mirabilis, when the infection is mild to moderate, including cases associated with concurrent bacteremia with these microorganisms.

Uncomplicated Skin and Skin Structure Infections caused by Staphylococcus aureus (methicillin-susceptible isolates only) or Streptococcus pyogenes.

Complicated Intra-abdominal Infections (used in combination with metronidazole) caused by Escherichia coli, viridans group streptococci, Pseudomonas aeruginosa, Klebsiellapneumoniae, Enterobacterspecies, or Bacteroidesfragilis. (See CLINICAL STUDIES.)

To reduce the development of drug-resistant bacteria and maintain the effectiveness of cefepime for injection, USP and other antibacterial drugs, cefepime for injection, USP should be used only to treat or prevent infections that are proven or strongly suspected to be caused by susceptible bacteria. When culture and susceptibility information are available, they should be considered in selecting or modifying antibacterial therapy. In the absence of such data, local epidemiology and susceptibility patterns may contribute to the empiric selection of therapy.

CLINICAL STUDIES

Febrile Neutropenic Patients

The safety and efficacy of empiric cefepime monotherapy of febrile neutropenic patients have been assessed in two multicenter, randomized trials comparing cefepime monotherapy (at a dose of 2 g intravenously every 8 hours) to ceftazidime monotherapy (at a dose of 2 g intravenously every 8 hours). These studies comprised 317 evaluable patients. Table 6 describes the characteristics of the evaluable patient population.

Table 6: Demographics of Evaluable Patients (First Episodes Only)
 | Cefepime | Ceftazidime
Total | 164 | 153
Median age (yr) | 56 (range, 18 to 82) | 55 (range, 16 to 84)
Male | 86 (52%) | 85 (56%)
Female | 78 (48%) | 68 (44%)
Leukemia | 65 (40%) | 52 (34%)
Other hematologic malignancies | 43 (26%) | 36 (24%)
Solid tumor | 54 (33%) | 56 (37%)
Median ANC nadir (cells/microliter) | 20 (range, 0 to 500) | 20 (range, 0 to 500)
Median duration of neutropenia (days) | 6 (range, 0 to 39) | 6 (range, 0 to 32)
Indwelling venous catheter | 97 (59%) | 86 (56%)
Prophylactic antibiotics | 62 (38%) | 64 (42%)
Bone marrow graft | 9 (5%) | 7 (5%)
SBP less than 90 mm Hg at entry | 7 (4%) | 2 (1%)
ANC = absolute neutrophil count; SBP = systolic blood pressure

Table 7 describes the clinical response rates observed. For all outcome measures, cefepime was therapeutically equivalent to ceftazidime.

Table 7: Pooled Response Rates for Empiric Therapy of Febrile Neutropenic Patients
 | % Response
 | Cefepime | Ceftazidime
Outcome Measures | (n=164) | (n=153)
Primary episode resolved with no treatment modification, no new febrile episodes or infection, and oral antibiotics allowed for completion of treatment | 51 | 55
Primary episode resolved with no treatment modification, no new febrile episodes or infection and no post-treatment oral antibiotics | 34 | 39
Survival, any treatment modification allowed | 93 | 97
Primary episode resolved with no treatment modification and oral antibiotics allowed for completion of treatment | 62 | 67
Primary episode resolved with no treatment modification and no post-treatment oral antibiotics | 46 | 51

Insufficient data exist to support the efficacy of cefepime monotherapy in patients at high risk for severe infection (including patients with a history of recent bone marrow transplantation, with hypotension at presentation, with an underlying hematologic malignancy, or with severe or prolonged neutropenia). No data are available in patients with septic shock.

Complicated Intra-Abdominal Infections

Patients hospitalized with complicated intra-abdominal infections participated in a randomized, double-blind, multicenter trial comparing the combination of cefepime (2 g every 12 hours) plus intravenous metronidazole (500 mg every 6 hours) versus imipenem/cilastatin (500 mg every 6 hours) for a maximum duration of 14 days of therapy. The study was designed to demonstrate equivalence of the two therapies. The primary analyses were conducted on the protocol-valid population, which consisted of those with a surgically confirmed complicated infection, at least one pathogen isolated pretreatment, at least 5 days of treatment, and a 4 to 6 week follow-up assessment for cured patients. Subjects in the imipenem/cilastatin arm had higher APACHE II scores at baseline. The treatment groups were otherwise generally comparable with regard to their pretreatment characteristics. The overall clinical cure rate among the protocol-valid patients was 81% (51 cured/63 evaluable patients) in the cefepime plus metronidazole group and 66% (62/94) in the imipenem/cilastatin group. The observed differences in efficacy may have been due to a greater proportion of patients with high APACHE II scores in the imipenem/cilastatin group.

CONTRAINDICATIONS

Cefepime for injection is contraindicated in patients who have shown immediate hypersensitivity reactions to cefepime or the cephalosporin class of antibiotics, penicillins or other beta-lactam antibiotics.

WARNINGS

Hypersensitivity Reactions to Cefepime, Cephalosporins, Penicillins, or Other Drugs

Before therapy with cefepime for injection is instituted, careful inquiry should be made to determine whether the patient has had previous immediate hypersensitivity reactions to cefepime, cephalosporins, penicillins, or other drugs. Exercise caution if this product is to be given to penicillin-sensitive patients because cross-hypersensitivity among beta-lactam antibiotics has been clearly documented and may occur in up to 10% of patients with a history of penicillin allergy. If an allergic reaction to cefepime for injection occurs, discontinue the drug.

Use in Patients with Renal Impairment

In patients with creatinine clearance less than or equal to 60 mL/min, adjust the dose of cefepime for injection to compensate for the slower rate of renal elimination [see DOSAGE AND ADMINISTRATION]. Because high and prolonged serum cefepime concentrations can occur from usual dosages in patients with renal impairment, the cefepime dosage should be reduced when it is administered to such patients. Continued dosage should be determined by degree of renal impairment, severity of infection, and susceptibility of the causative organisms.

Neurotoxicity

During postmarketing surveillance, serious adverse reactions have been reported including life-threatening or fatal occurrences of the following: encephalopathy (disturbance of consciousness including confusion, hallucinations, stupor, and coma), myoclonus, seizures, and non-convulsive status epilepticus (see ADVERSE REACTIONS: Postmarketing Experience). Most cases occurred in patients with renal impairment who did not receive appropriate dosage adjustment. However, some cases of neurotoxicity occurred in patients receiving a dosage adjustment appropriate for their degree of renal impairment. In the majority of cases, symptoms of neurotoxicity were reversible and resolved after discontinuation of cefepime and/or after hemodialysis. If neurotoxicity associated with cefepime therapy occurs, consider discontinuing cefepime or making appropriate dosage adjustments in patients with renal impairment.

Clostridium difficile associated diarrhea (CDAD) has been reported with use of nearly all antibacterial agents, including cefepime for injection, and may range in severity from mild diarrhea to fatal colitis. Treatment with antibacterial agents alters the normal flora of the colon leading to overgrowth of C. difficile.

C. difficile produces toxins A and B, which contribute to the development of CDAD. Hypertoxin-producing strains of C. difficile cause increased morbidity and mortality, as these infections can be refractory to antimicrobial therapy and may require colectomy. CDAD must be considered in all patients who present with diarrhea following antibiotic use. Careful medical history is necessary since CDAD has been reported to occur over two months after the administration of antibacterial agents.

If CDAD is suspected or confirmed, ongoing antibiotic use not directed against C. difficile may need to be discontinued. Appropriate fluid and electrolyte management, protein supplementation, antibiotic treatment of C. difficile, and surgical evaluation should be instituted as clinically indicated.

PRECAUTIONS

General

Prescribing cefepime for injection in the absence of a proven or strongly suspected bacterial infection or a prophylactic indication is unlikely to provide benefit to the patient and increases the risk of the development of drug-resistant bacteria.

As with other antimicrobials, prolonged use of cefepime for injection may result in overgrowth of non-susceptible microorganisms. Repeated evaluation of the patient’s condition is essential. Should superinfection occur during therapy, appropriate measures should be taken.

Many cephalosporins, including cefepime, have been associated with a fall in prothrombin activity. Those at risk include patients with renal or hepatic impairment, or poor nutritional state, as well as patients receiving a protracted course of antimicrobial therapy. Prothrombin time should be monitored in patients at risk, and exogenous vitamin K administered as indicated.

Positive direct Coombs’ tests have been reported during treatment with cefepime for injection. In hematologic studies or in transfusion cross-matching procedures when antiglobulin tests are performed on the minor side or in Coombs’ testing of newborns whose mothers have received cephalosporin antibiotics before parturition, it should be recognized that a positive Coombs’ test may be due to the drug.

Cefepime for injection should be prescribed with caution in individuals with a history of gastrointestinal disease, particularly colitis.

Arginine has been shown to alter glucose metabolism and elevate serum potassium transiently when administered at 33 times the amount provided by the maximum recommended human dose of cefepime for injection. The effect of lower doses is not presently known.

Information for Patients

Before therapy with cefepime for injection is instituted, careful inquiry should be made to determine whether the patient has had previous immediate hypersensitivity reactions to cefepime, cephalosporins, penicillins, or other drugs. Exercise caution if this product is to be given to penicillin-sensitive patients because cross-hypersensitivity among beta-lactam antibiotics has been clearly documented and may occur in up to 10% of patients with a history of penicillin allergy. If an allergic reaction to cefepime for injection occurs, discontinue the drug. Serious acute hypersensitivity reactions may require treatment with epinephrine and other emergency measures including oxygen, corticosteroids, intravenous fluids, intravenous antihistamines, pressor amines, and airway management, as clinically indicated.

Patients should be counseled that antibacterial drugs including cefepime for injection should only be used to treat bacterial infections. They do not treat viral infections (e.g., the common cold). When cefepime for injection is prescribed to treat a bacterial infection, patients should be told that although it is common to feel better early in the course of therapy, the medication should be taken exactly as directed. Skipping doses or not completing the full course of therapy may (1) decrease the effectiveness of the immediate treatment and (2) increase the likelihood that bacteria will develop resistance and will not be treatable by cefepime for injection or other antibacterial drugs in the future.

Diarrhea is a common problem caused by antibiotics, which usually ends when the antibiotic is discontinued. Sometimes after starting treatment with antibiotics, patients can develop watery and bloody stools (with or without stomach cramps and fever) even as late as two or more months after having taken the last dose of the antibiotic. If this occurs, patients should contact their physician as soon as possible.

Patients should be advised of neurological adverse events that could occur with cefepime for injection use. Patients should be instructed to inform their healthcare provider at once of any neurological signs and symptoms, including encephalopathy (disturbance of consciousness including confusion, hallucinations, stupor, and coma), myoclonus, seizures, and non-convulsive status epilepticus for immediate treatment, dosage adjustment, or discontinuation of cefepime for injection.

Drug Interactions

Renal function should be monitored carefully if high doses of aminoglycosides are to be administered with cefepime for injection because of the increased potential of nephrotoxicity and ototoxicity of aminoglycoside antibiotics. Nephrotoxicity has been reported following concomitant administration of other cephalosporins with potent diuretics such as furosemide.

Drug/Laboratory Test Interactions

The administration of cefepime may result in a false-positive reaction for glucose in the urine when using Clinitest™ tablets. It is recommended that glucose tests based on enzymatic glucose oxidase reactions (such as Clinistix™) be used.

Carcinogenesis, Mutagenesis, Impairment of Fertility

No animal carcinogenicity studies have been conducted with cefepime. In chromosomal aberration studies, cefepime was positive for clastogenicity in primary human lymphocytes, but negative in Chinese hamster ovary cells. In other in vitro assays (bacterial and mammalian cell mutation, DNA repair in primary rat hepatocytes, and sister chromatid exchange in human lymphocytes), cefepime was negative for genotoxic effects. Moreover, in vivo assessments of cefepime in mice (2 chromosomal aberration and 2 micronucleus studies) were negative for clastogenicity. No untoward effects on fertility were observed in rats when cefepime was administered subcutaneously at doses up to 1000 mg/kg/day (1.6 times the recommended maximum human dose calculated on a mg/m^2 basis).

Pregnancy

Teratogenic Effects

Pregnancy Category B

Cefepime was not teratogenic or embryocidal when administered during the period of organogenesis to rats at doses up to 1000 mg/kg/day (1.6 times the recommended maximum human dose calculated on a mg/m^2 basis) or to mice at doses up to 1200 mg/kg (approximately equal to the recommended maximum human dose calculated on a mg/m^2 basis) or to rabbits at a dose level of 100 mg/kg (0.3 times the recommended maximum human dose calculated on a mg/m^2 basis).

There are, however, no adequate and well-controlled studies of cefepime use in pregnant women. Because animal reproduction studies are not always predictive of human response, this drug should be used during pregnancy only if clearly needed.

Nursing Mothers

Cefepime is excreted in human breast milk in very low concentrations (0.5 mcg/mL). Caution should be exercised when cefepime is administered to a nursing woman.

Labor and Delivery

Cefepime has not been studied for use during labor and delivery. Treatment should only be given if clearly indicated.

Pediatric Use

The safety and effectiveness of cefepime in the treatment of uncomplicated and complicated urinary tract infections (including pyelonephritis), uncomplicated skin and skin structure infections, pneumonia, and as empiric therapy for febrile neutropenic patients have been established in the age groups 2 months up to 16 years. Use of cefepime for injection in these age groups is supported by evidence from adequate and well-controlled studies of cefepime in adults with additional pharmacokinetic and safety data from pediatric trials (see CLINICAL PHARMACOLOGY).

Safety and effectiveness in pediatric patients below the age of 2 months have not been established. There are insufficient clinical data to support the use of cefepime for injection in pediatric patients under 2 months of age or for the treatment of serious infections in the pediatric population where the suspected or proven pathogen is Haemophilusinfluenzae type b.

IN THOSE PATIENTS IN WHOM MENINGEAL SEEDING FROM A DISTANT INFECTION SITE OR IN WHOM MENINGITIS IS SUSPECTED OR DOCUMENTED, AN ALTERNATE AGENT WITH DEMONSTRATED CLINICAL EFFICACY IN THIS SETTING SHOULD BE USED.

Geriatric Use

Of the more than 6400 adults treated with cefepime for injection in clinical studies, 35% were 65 years or older while 16% were 75 years or older. When geriatric patients received the usual recommended adult dose, clinical efficacy and safety were comparable to clinical efficacy and safety in non-geriatric adult patients.

Serious adverse events have occurred in geriatric patients with renal insufficiency given unadjusted doses of cefepime, including life-threatening or fatal occurrences of the following: encephalopathy, myoclonus, and seizures. (See WARNINGS and ADVERSE REACTIONS.) This drug is known to be substantially excreted by the kidney, and the risk of toxic reactions to this drug may be greater in patients with impaired renal function. Because elderly patients are more likely to have decreased renal function, care should be taken in dose selection, and renal function should be monitored. (See CLINICAL PHARMACOLOGY: Specific Populations, WARNINGS, and DOSAGE AND ADMINISTRATION.)

ADVERSE REACTIONS

Clinical Trials

Because clinical trials are conducted under widely varying conditions, adverse reaction rates observed in clinical trials of a drug cannot be directly compared to rates in the clinical trials of another drug and may not reflect the rates observed in practice.

In clinical trials using multiple doses of cefepime, 4137 patients were treated with the recommended dosages of cefepime (500 mg to 2 g intravenous every 12 hours). There were no deaths or permanent disabilities thought related to drug toxicity. Sixty-four (1.5%) patients discontinued medication due to adverse events thought by the investigators to be possibly, probably, or almost certainly related to drug toxicity. Thirty-three (51%) of these 64 patients who discontinued therapy did so because of rash. The percentage of cefepime-treated patients who discontinued study drug because of drug-related adverse events was very similar at daily doses of 500 mg, 1 g, and 2 g every 12 hours (0.8%, 1.1%, and 2%, respectively). However, the incidence of discontinuation due to rash increased with the higher recommended doses.

The following adverse events (Table 8) were thought to be probably related to cefepime during evaluation of the drug in clinical trials conducted in North America (n=3125 cefepime-treated patients).

Table 8: Adverse Reactions Cefepime Multiple-Dose Dosing Regimens Clinical Trials – North America
INCIDENCE EQUAL TO OR GREATER THAN 1% | Local reactions (3%), including phlebitis (1.3%), pain and/or inflammation (0.6%) [Local reactions, irrespective of relationship to cefepime in those patients who received intravenous infusion (n=3048).] ; rash (1.1%)
INCIDENCE LESS THAN 1% BUT GREATER THAN 0.1% | Colitis (including pseudomembranous colitis), diarrhea, erythema, fever, headache, nausea, oral moniliasis, pruritus, urticaria, vaginitis, vomiting, anemia

At the higher dose of 2 g every 8 hours, the incidence of probably-related adverse events was higher among the 795 patients who received this dose of cefepime. They consisted of rash (4%), diarrhea (3%), nausea (2%), vomiting (1%), pruritus (1%), fever (1%), and headache (1%).

The following (Table 9) adverse laboratory changes, irrespective of relationship to therapy with cefepime, were seen during clinical trials conducted in North America.

Table 9: Adverse Laboratory Changes Cefepime Multiple-Dose Dosing Regimens Clinical Trials – North America
INCIDENCE EQUAL TO OR GREATER THAN 1% | Positive Coombs’ test (without hemolysis) (16.2%); decreased phosphorus (2.8%); increased ALT/SGPT (2.8%), AST/SGOT (2.4%), eosinophils (1.7%); abnormal PTT (1.6%), PT (1.4%)
INCIDENCE LESS THAN 1% BUT GREATER THAN 0.1% | Increased alkaline phosphatase, BUN, calcium, creatinine, phosphorus, potassium, total bilirubin; decreased calcium [Hypocalcemia was more common among elderly patients. Clinical consequences from changes in either calcium or phosphorus were not reported.] , hematocrit, neutrophils, platelets, WBC

A similar safety profile was seen in clinical trials of pediatric patients (see PRECAUTIONS: Pediatric Use).

Postmarketing Experience

In addition to the events reported during North American clinical trials with cefepime, the following adverse experiences have been reported during worldwide postmarketing experience.

Encephalopathy (disturbance of consciousness including confusion, hallucinations, stupor, and coma), myoclonus, seizures, and non-convulsive status epilepticus have been reported. Although most cases occurred in patients with renal impairment who received doses of cefepime that exceeded the recommended dosage schedules, some cases of neurotoxicity occurred in patients receiving an appropriate dosage adjustment for their degree of renal impairment. If neurotoxicity associated with cefepime therapy occurs, consider discontinuing cefepime or making appropriate dosage adjustments in patients with renal impairment. (see WARNINGS.)

As with other cephalosporins, anaphylaxis including anaphylactic shock, transient leukopenia, neutropenia, agranulocytosis and thrombocytopenia have been reported.

Cephalosporin-Class Adverse Reactions

In addition to the adverse reactions listed above that have been observed in patients treated with cefepime, the following adverse reactions and altered laboratory tests have been reported for cephalosporin-class antibiotics: Stevens-Johnson syndrome, erythema multiforme, toxic epidermal necrolysis, renal dysfunction, toxic nephropathy, aplastic anemia, hemolytic anemia, hemorrhage, hepatic dysfunction including cholestasis, and pancytopenia.

OVERDOSAGE

Patients who receive an overdose should be carefully observed and given supportive treatment. In the presence of renal insufficiency, hemodialysis, not peritoneal dialysis, is recommended to aid in the removal of cefepime from the body. Accidental overdosing has occurred when large doses were given to patients with impaired renal function. Symptoms of overdose include encephalopathy (disturbance of consciousness including confusion, hallucinations, stupor, and coma), myoclonus, seizures, neuromuscular excitability and non-convulsive status epilepticus. (See WARNINGS, ADVERSE REACTIONS, and DOSAGE AND ADMINISTRATION.)

DOSAGE AND ADMINISTRATION

The recommended adult and pediatric dosages and routes of administration are outlined in the following table 10. Cefepime for injection should be administered intravenously over approximately 30 minutes.

Table 10: Recommended Dosage Schedule for Cefepime for Injection in Patients with CrCL Greater Than 60 mL/min [Adjust dose in patients with CrCL less than or equal to 60 mL/min]
Site and Type of Infection | Dose | Frequency | Duration (days)
Adults
Moderate to Severe Pneumonia due to S. pneumoniae [including cases associated with concurrent bacteremia.] , P. aeruginosa [For Pseudomonas aeruginosa, use 2 g IV every 8 hours (50 mg per kg per dose in pediatric patients 2 months up to 16 years)] , K. pneumoniae, or Enterobacter species | 1 to 2 g IV | Every 8 to 12 hours | 10
Empiric therapy for febrile neutropenic patients (See INDICATIONS AND USAGE and CLINICAL STUDIES.) | 2 g IV | Every 8 hours | 7 [or until resolution of neutropenia. In patients whose fever resolves but who remain neutropenic for more than 7 days, the need for continued antimicrobial therapy should be re-evaluated frequently.]
Mild to Moderate Uncomplicated or Complicated Urinary Tract Infections, including pyelonephritis, due to E. coli, K. pneumoniae, or P. mirabilis | 0.5 to 1 g IV/IM [Intramuscular route of administration is indicated only for mild to moderate, uncomplicated or complicated UTIs due to E. coli when the intramuscular route is considered to be a more appropriate route of drug administration.] | Every 12 hours | 7 to 10
Severe Uncomplicated or Complicated Urinary Tract Infections, including pyelonephritis, due to E. coli or K. pneumoniae | 2 g IV | Every 12 hours | 10
Moderate to Severe Uncomplicated Skin and Skin Structure Infections due to S. aureus or S. pyogenes | 2 g IV | Every 12 hours | 10
Complicated Intra-abdominal Infections (used in combination with metronidazole) caused by E. coli, viridans group streptococci, P. aeruginosa, K. pneumoniae, Enterobacterspecies, or B. fragilis. (See CLINICAL STUDIES.) | 2 g IV | Every 8 to 12 hours | 7 to 10
Pediatric Patients (2 months up to 16 years)
The maximum dose for pediatric patients should not exceed the recommended adult dose.
The usual recommended dosage in pediatric patients up to 40 kg in weight for uncomplicated and complicated urinary tract infections (including pyelonephritis), uncomplicated skin and skin structure infections, and pneumonia is 50 mg per kg per dose, administered every 12 hours (50 mg per kg per dose, every 8 hours for febrile neutropenic patients), for durations as given above.

Patients with Hepatic Impairment

No adjustment is necessary for patients with hepatic impairment.

Patients with Renal Impairment

In patients with creatinine clearance less than or equal to 60 mL/min, the dose of cefepime for injection should be adjusted to compensate for the slower rate of renal elimination. The recommended initial dose of cefepime for injection should be the same as in patients with normal renal function except in patients undergoing hemodialysis. The recommended doses of cefepime for injection in patients with renal impairment are presented in Table 11.

When only serum creatinine is available, the following formula (Cockcroft and Gault equation)^4 may be used to estimate creatinine clearance. The serum creatinine should represent a steady state of renal function:

Males: Creatinine Clearance (mL/min) = | Weight (kg) × (140-age)
Males: Creatinine Clearance (mL/min) = | 72 × serum creatinine (mg/dL)

Females: 0.85 × above value

Table 11: Recommended Dosing Schedule for Cefepime for Injection in Adult Patients (Normal Renal Function, Renal Impairment, and Hemodialysis)
Creatinine Clearance (mL/min) | Recommended Maintenance Schedule
Greater than 60 Normal recommended dosing schedule | 500 mg every 12 hours | 1 g every 12 hours | 2 g every 12 hours | 2 g every 8 hours
30 to 60 | 500 mg every 24 hours | 1 g every 24 hours | 2 g every 24 hours | 2 g every 12 hours
11 to 29 | 500 mg every 24 hours | 500 mg every 24 hours | 1 g every 24 hours | 2 g every 24 hours
Less than 11 | 250 mg every 24 hours | 250 mg every 24 hours | 500 mg every 24 hours | 1 g every 24 hours
CAPD | 500 mg every 48 hours | 1 g every 48 hours | 2 g every 48 hours | 2 g every 48 hours
Hemodialysis [On hemodialysis days, cefepime should be administered following hemodialysis. Whenever possible, cefepime should be administered at the same time each day.] | 1 g on day 1, then 500 mg every 24 hours thereafter |  |  | 1 g every 24 hours

In patients undergoing continuous ambulatory peritoneal dialysis, cefepime for injection may be administered at normally recommended doses at a dosage interval of every 48 hours (see Table 11).

In patients undergoing hemodialysis, approximately 68% of the total amount of cefepime present in the body at the start of dialysis will be removed during a 3-hour dialysis period. The dosage of cefepime for injection for hemodialysis patients is 1 g on Day 1 followed by 500 mg every 24 hours for the treatment of all infections except febrile neutropenia, which is 1 g every 24 hours.

Cefepime for injection should be administered at the same time each day and following the completion of hemodialysis on hemodialysis days (see Table 11).

Data in pediatric patients with impaired renal function are not available; however, since cefepime pharmacokinetics are similar in adults and pediatric patients (see CLINICAL PHARMACOLOGY), changes in the dosing regimen proportional to those in adults (see Tables 10 and 11) are recommended for pediatric patients.

Administration

For Intravenous Infusion

Dilute with a suitable parenteral vehicle prior to intravenous infusion. Constitute the 1 g, or 2 g vial, and add an appropriate quantity of the resulting solution to an intravenous container with one of the compatible intravenous fluids listed in the Compatibility and Stability subsection. THE RESULTING SOLUTION SHOULD BE ADMINISTERED OVER APPROXIMATELY 30 MINUTES.

Intermittent intravenous infusion with a Y-type administration set can be accomplished with compatible solutions. However, during infusion of a solution containing cefepime, it is desirable to discontinue the other solution.

Intramuscular Administration

For intramuscular administration, cefepime for injection should be constituted with one of the following diluents: Sterile Water for Injection, 0.9% Sodium Chloride, 5% Dextrose Injection, 0.5% or 1% Lidocaine Hydrochloride, or Sterile Bacteriostatic Water for Injection with Parabens or Benzyl Alcohol (refer to Table 12).

Preparation of cefepime for injection solutions is summarized in Table 12.

Table 12: Preparation of Solutions of Cefepime for Injection
Single-Dose Vials for Intravenous/Intramuscular Administration | Amount of Diluent to be added (mL) | Approximate Available Volume (mL) | Approximate Cefepime Concentration (mg/mL)
cefepime vial content
1 g (IV) | 10 | 11.3 | 100
1 g (IM) | 2.4 | 3.6 | 280
2 g (IV) | 10 | 12.5 | 160

Compatibility and Stability

Intravenous

Cefepime for injection is compatible at concentrations between 1 mg per mL and 40 mg per mL with the following intravenous infusion fluids: 0.9% Sodium Chloride Injection, 5% and 10% Dextrose Injection, M/6 Sodium Lactate Injection, 5% Dextrose and 0.9% Sodium Chloride Injection, Lactated Ringers and 5% Dextrose Injection, Normosol™-R, and Normosol™-M in 5% Dextrose Injection. These solutions may be stored up to 24 hours at controlled room temperature 20° C to 25° C (68° F to 77° F) or 7 days in a refrigerator 2° C to 8° C (36° F to 46° F).

Cefepime for injection admixture compatibility information is summarized in Table 13.

Table 13: Cefepime Admixture Stability
 |  |  | Stability Time for
Cefepime for Injection Concentration | Admixture and Concentration | IV Infusion Solutions | RT/L (20° to 25° C) | Refrigeration (2° to 8° C)
40 mg/mL | Amikacin 6 mg/mL | NS or D5W | 24 hours | 7 days
40 mg/mL | Ampicillin 1 mg/mL | D5W | 8 hours | 8 hours
40 mg/mL | Ampicillin 10 mg/mL | D5W | 2 hours | 8 hours
40 mg/mL | Ampicillin 1 mg/mL | NS | 24 hours | 48 hours
40 mg/mL | Ampicillin 10 mg/mL | NS | 8 hours | 48 hours
4 mg/mL | Ampicillin 40 mg/mL | NS | 8 hours | 8 hours
4 to 40 mg/mL | Clindamycin Phosphate 0.25 to 6 mg/mL | NS or D5W | 24 hours | 7 days
4 mg/mL | Heparin 10 to 50 units/mL | NS or D5W | 24 hours | 7 days
4 mg/mL | Potassium Chloride 10 to 40 mEq/L | NS or D5W | 24 hours | 7 days
4 mg/mL | Theophylline 0.8 mg/mL | D5W | 24 hours | 7 days
1 to 4 mg/mL | na | Aminosyn™ II 4.25% with electrolytes and calcium | 8 hours | 3 days
0.125 to 0.25 mg/mL | na | Inpersol™ with 4.25% dextrose | 24 hours | 7 days
NS = 0.9% Sodium Chloride Injection
D5W = 5% Dextrose Injection
na = not applicable
RT/L = Ambient room temperature and light

Solutions of cefepime for injection, like those of most beta-lactam antibiotics, should not be added to solutions of ampicillin at a concentration greater than 40 mg per mL, and should not be added to metronidazole, vancomycin, gentamicin, tobramycin, netilmicin sulfate, or aminophylline because of potential interaction. However, if concurrent therapy with cefepime for injection is indicated, each of these antibiotics can be administered separately.

Intramuscular

Cefepime for injection constituted as directed is stable for 24 hours at controlled room temperature 20° C to 25° C (68° F to 77° F) or for 7 days in a refrigerator 2° C to 8° C (36° F to 46° F) with the following diluents: Sterile Water for Injection, 0.9% Sodium Chloride Injection, 5% Dextrose Injection, Sterile Bacteriostatic Water for Injection with Parabens or Benzyl Alcohol, or 0.5% or 1% Lidocaine Hydrochloride.

NOTE: PARENTERAL DRUGS SHOULD BE INSPECTED VISUALLY FOR PARTICULATE MATTER BEFORE ADMINISTRATION. IF PARTICULATE MATTER IS EVIDENT IN RECONSTITUTED FLUIDS, THE DRUG SOLUTION SHOULD BE DISCARDED.

As with other cephalosporins, the color of cefepime for injection powder, as well as its solutions, tend to darken depending on storage conditions; however, when stored as recommended, the product potency is not adversely affected.

HOW SUPPLIED

Cefepime for injection, USP is supplied as follows:

Cefepime for injection, USP in the dry state, is a white to pale yellow powder. Constituted solution of cefepime for injection, USP can range in color from pale yellow to amber.

1 g [Based on cefepime activity] vial | (tray of 10) | NDC 0781-3222-95
2 g vial | (tray of 10) | NDC 0781-3223-95

Storage

IN THE DRY STATE STORE AT 20° TO 25°C (68° TO 77°F) [SEE USP CONTROLLED ROOM TEMPERATURE]. PROTECT FROM LIGHT. RETAIN IN CARTON UNTIL TIME OF USE.

REFERENCES

1. Clinical and Laboratory Standards Institute (CLSI). Methods for Dilution Antimicrobial Susceptibility Tests for Bacteria that Grow Aerobically; Approved Standard - Ninth Edition. CLSI document M07-A9, Clinical and Laboratory Standards Institute, 950 West Valley Road, Suite 2500, Wayne, Pennsylvania 19087, USA, 2012.
2. Clinical and Laboratory Standards Institute (CLSI). Performance Standards for Antimicrobial Susceptibility Testing; Twenty-third Informational Supplement, CLSI document M100-S23.CLSI document M100-S23, Clinical and Laboratory Standards Institute, 950 West Valley Road, Suite 2500, Wayne, Pennsylvania 19087, USA, 2013.
3. Clinical and Laboratory Standards Institute (CLSI). Performance Standards for Antimicrobial Disk Diffusion Susceptibility Tests; Approved Standard – Eleventh Edition. CLSI document M02-A11, Clinical and Laboratory Standards Institute, 950 West Valley Road, Suite 2500, Wayne, Pennsylvania 19087, USA, 2012.
4. Cockcroft DW, Gault MH. Prediction of creatinine clearance from serum creatinine. Nephron. 1976; 16:31-41.

June 2014

ABL3810BU1

Manufactured by

Antibióticos do Brasil Ltda.

Rod. Professor Zeferino Vaz, SP - 332, km 135

Cosmópolis/SP - Brazil

for Sandoz Inc., Princeton, NJ 08540

1 gram Label

NDC 0781-3222-95

Cefepime for Injection, USP

1 gram / Vial

For IV or IM use after constitution.

Rx only

1 Box - 10 Vials

SANDOZ

2 gram Label

NDC 0781-3223-95

Cefepime for Injection, USP

2 grams / Vial

For IV use after constitution.

Rx only

1 Box – 10 vials

SANDOZ